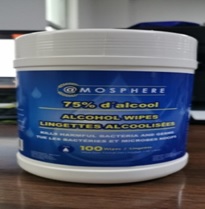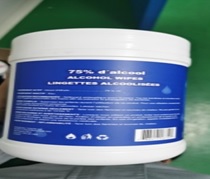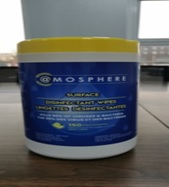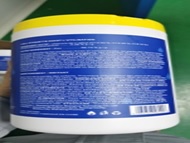 DRUG LABEL: Sanitary wipes
NDC: 81332-102 | Form: CLOTH
Manufacturer: Shandong Green Huineng Technology Co., Ltd.
Category: otc | Type: HUMAN OTC DRUG LABEL
Date: 20230619

ACTIVE INGREDIENTS: DIDECYLDIMONIUM CHLORIDE 0.00168 mg/1 1; BENZALKONIUM CHLORIDE 0.00189 mg/1 1
INACTIVE INGREDIENTS: WATER

75% alcohol sanitary wipes; Sanitary wipes

75% alcohol sanitary wipes

Sanitary wipes

Active Ingredient(s)

75% alcohol sanitary wipes: Alcohol 3.15mL/pcs. Purpose: Antiseptic

Sanitary wipes: Didecyl dimethyl ammonium chloride 0.00168mg/pcs; benzalkonium chloride 0.00189mg/pcs Purpose: Antiseptic

Purpose

Antiseptic

Use

75% alcohol sanitary wipes, Sanitary wipes to help reduce bacteria that potentially can cause disease. For use when soap and water are not available.

Warnings

For external use only.

Do not use

- in children less than 2 months of age
- on open skin wounds

When using this product keep out of eyes, ears, and mouth. In case of contact with eyes, rinse eyes thoroughly with water.
Stop use and ask a doctor if irritation or rash occurs. These may be signs of a serious condition.
Keep out of reach of children. If swallowed, get medical help or contact a Poison Control Center right away.

Stop use and ask a doctor if irritation or rash occurs. These may be signs of a serious condition.

Keep out of reach of children. If swallowed, get medical help or contact a Poison Control Center right away.

Directions

- Wipe the surface of the skin and let it dry naturally.
- Supervise children under 6 years of age when using this product to avoid swallowing.

Other information

- Store between 15-30C (59-86F)
- Avoid freezing and excessive heat above 40C (104F)

Inactive ingredients

75% alcohol sanitary wipes:

WATER

Sanitary wipes:

WATER